DRUG LABEL: Standardized Bermuda Grass Pollen
NDC: 49288-0063 | Form: INJECTION, SOLUTION
Manufacturer: Antigen Laboratories, Inc.
Category: prescription | Type: HUMAN PRESCRIPTION DRUG LABEL
Date: 20090810

ACTIVE INGREDIENTS: CYNODON DACTYLON POLLEN 10000 [BAU]/1 mL
INACTIVE INGREDIENTS: Glycerin 0.525 mL/1 mL; Water; Sodium Chloride 0.0095 g/1 mL; Sodium Bicarbonate 0.0024 g/1 mL

ALLERGENIC EXTRACT

WARNINGS
Standardized Grass Pollen extracts labeled in Bioequivalent Allergy Units (BAU/ml) are not interchangeable with grass extracts labeled in Allergy Units (AU/ml) or with non-standardized grass pollen extracts. Standardized Grass Pollen allergenic extract is intended for use by physicians or under the guidance of physicians who are experienced in the administration of allergenic extracts for diagnosis and/or immunotherapy and in emergency care of anaphylaxis. Standardized Grass Pollen extracts are not interchangeable with other allergenic extracts. Patients being switched from other manufacturers' extracts to Antigen Laboratories' allergenic extracts should have their dose adjusted. (See "WARNINGS" and "DOSAGE AND ADMINISTRATION" sections.)
Caution is imperative when switching from non-standardized grass pollen to Standardized Grass Pollen extracts. Standardized Grass Pollens may have equal, greater, or lesser potency than non-standardized grass pollen. Refer to "CLINICAL PHARMACOLOGY" Table 2 and "DOSAGE AND ADMINISTRATION" sections.
Severe systemic reactions may occur with all allergenic extracts. In certain individuals, these Iife-threatening reactions may result in death. Patients should be observed for at least 20 minutes following allergenic extract injections. Treatment and emergency measures, as well as personnel trained in their use, must be available in the event of a life-threatening reaction. Sensitive patients may experience severe anaphylactic reactions resulting in respiratory obstruction, shock, coma and/or death. Report serious adverse events to MedWatch, 5600 Fishers Lane, Rockville, MD 20852-9787, phone 1-800-FDA-1088.
Extreme caution must be exercised in treating patients with steroid dependent or labile asthma, chronic obstructive pulmonary disease, and cardiovascular disease.
Patients being switched from one lot of extract to another lot from the same manufacturer, should have dose reduced by 75%.
Allergenic extracts should not be injected intravenously. Deep subcutaneous routes have proven to be safe. See the "WARNINGS", "PRECAUTIONS", "ADVERSE REACTIONS" and "OVERDOSAGE" sections.
Patients receiving beta-blockers may not be responsive to epinephrine or inhaled bronchodilators. Patients with respiratory obstruction not responding to parenteral or inhaled bronchodilators may require theophylline, oxygen, intubation and Iife support systems. Parenteral fluid and/or plasma expanders may be utilized for treatment of shock. Adrenocorticosteroids may be administered parenterally or intravenously. Refer to "ADVERSE REACTIONS" section.

DESCRIPTION
Antigen Laboratories' Standardized Grass Pollen allergenic extracts are sterile and intended for dilution prior to skin testing and/or immunotherapy. The route of administration for immunotherapy is subcutaneous. The routes of administration for diagnostic purposes are intradermal or prick-puncture of the skin. Standardized Grass Pollen allergenic extract labeled in BAU/ml is not interchangeable with grass pollen extract labeled in AU/ml or with non-standardized grass pollen extract.
Potency of Standardized Grass Pollen allergenic extract is determined by comparison to a Center for Biologics Evaluation and Research (CBER) approved reference. References are available for pollen extracts of Orchard Grass (Dactylis glomerata), Perennial Rye Grass (Lolium perenne), Timothy Grass (Phleum pratense), Redtop Grass (Agrostis alba), Kentucky (June) Bluegrass (Poa pratensis), Bermuda Grass (Cynodon dactylon), Meadow Fescue Grass (Festuca elatior), and Sweet Vernal Grass (Anthoxanthum odoratum). Quantitative skin testing is used by CBER to establish reference's potency as Bioequivalent Allergy Units (BAU). CBER reference labeled 10,000 BAU/ml produces a sum of erythema diameter of 50 mm with highly puncture reactive subjects at an intradermal dilution of approximately 1:500,000.^11,17 CBER references labeled 100,000 BAU/ml produce a SumE=50 mm at an intradermal dilution of 1:5,000,000. Relative potency of Standardized Grass Pollen allergenic extracts to CBER reference is determined by Enzyme-linked Immunosorbent Assay (ELISA).

In addition to relative potency testing of Standardized Grass Pollen extract the following testing is performed:
1. Microscopic examination to confirm identity and purity of source pollens.
2. lsoelectric focusing (IEF) pattern of source material is compared to respective CBER
reference extract.
3. lsoelectric focusing pattern of final 100,000 BAU/ml (10,000 BAU/ml Bermuda Grass) product is compared to CBER reference extract.
4. Ninhydrin Protein Analysis.
5. Glycerine Analysis. (A minimum of 50% v/v glycerine for optimal stability during the entire
dating period.)
6. Sterility Testing.
7. Animal Safety Testing.
Standardized Grass Pollen allergenic extracts are extracted at 1:10 weight to volume (w/v) ratio of source material to extraction fluid. Bermuda Grass is only available in 10,000 BAU/ml. Standardized Grass Pollen extracts are diluted after extraction to fall in acceptable relative potency range for a 100,000 BAU/ml or 10,000 BAU/ml (Bermuda Grass) product. Standardized Grass Pollen allergenic extracts (except Bermuda) of 10,000 BAU/ml potency are prepared by diluting the 100,000 BAU/ml extract 1:10 with extracting fluid.
Various mixtures of eight Standardized Grass Pollen extracts are available. Mixtures of Standardized Grass Pollen extracts with non-standardized grass pollen extracts are available. Concentrations of Standardized Grass Pollen extracts (BAU/ml) and non-standardized grass pollen extracts (w/v) in a mixture are printed on the last page of this circular, if applicable.
Active Ingredients: Allergens are described by common and scientific name on container label or last page of this circular. Preservative is 50% v/v glycerine. Inactive ingredients are 0.95% sodium chloride, 0.24% sodium bicarbonate and water for injection.

CLINICAL PHARMACOLOGY
Studies indicate allergic individuals produce immunoglobulins of the IgE class in response to exposure to grass pollens. Subsequent exposure to grass pollen results in a combination of allergen with IgE antibody fixed on mast cells or basophil membranes. This cross-linking results in stimulation of mast cell which leads to release and generation of pharmacologically active substances that produce immediate hypersensitivity reaction.^15
The mode of action of immunotherapy with allergenic extracts is still being investigated. Subcutaneous injections of increasing doses of allergenic extract into patients with allergic disease have been shown to result in both humoral and cellular changes. These include production of allergen specific IgG antibodies, suppression of histamine release from target cells, decrease in circulating levels of antigen specific IgE antibody over long periods of time and suppression of peripheral blood T-Iymphocyte cell responses to antigen. ^5,9,10
Puncture and intradermal data from skin testing with CBER grass reference is summarized in Table 1. Fifteen patients with clinical symptoms when exposed to grass pollen were included in the study. The mean sum erythema (PSumE) and mean sum wheal (PSumW) from puncture testing is listed in Table 1A. The Intradermal Dilution for 50 mm Sum of Erythema determines Bioequivalent ALlergy Units (ID50EAL) method was used by CBER personnel to calculate intradermal dose (BAU/ml). The calculated mean and ranges of intradermal dose (BAU/ml) for 50 mm sum of erythema using reference extract is summarized in Table 1B. ^17

TABLE 1
Puncture and Intradermal Data with CBER Grass Reference
A. Puncture Data with 10,000 BAU/ml Grass Extracts (Bifurcated needle)

Reference Pollen | FDA Lot # | N | PSumE (mm) Mean | PSumE (mm) Range | PSumW (mm) Mean | PSumW (mm) Range
Bermuda | E4-Ber | 15 | 90.3 | 43-123 | 15.7 | 7-31
June | E3-Jkb | 15 | 77.3 | 47-107 | 15.9 | 6-28
Meadow Fescue | E4-Mf | 15 | 81.1 | 57-115 | 11.9 | 7-22
Orchard | E4-Or | 15 | 84.3 | 57-111 | 14.1 | 9-19
Perennial Rye | E10-Rye | 15 | 92.3 | 73-135 | 17.5 | 6-36
Redtop | E4-Rt | 15 | 77.1 | 42-98 | 14.1 | 8-19
Sweet Vernal | E4-Sv | 15 | 81.2 | 28-123 | 15.7 | 8-30
Timothy | E6-Ti | 15 | 88.3 | 51-109 | 16.9 | 8-40

B. Calculated Intradermal Dose (BAU50) of CBER Grass Reference for 50mm Sum of Erythema.

Reference Pollen | FDA Lot # | BAU50/ml Mean | BAU50/ml Range
Bermuda | E4-Ber | 0.02 | 0.4-0.0003
June | E3-Jkb | 0.02 | 0.1-0.004
Meadow Fescue | E4-Mf | 0.02 | 0.9-0.002
Orchard | E4-Or | 0.02 | 1.9-0.002
Perennial Rye | E10-Rye | 0.02 | 0.7-0.002
Redtop | E4-Rt | 0.02 | 0.8-0.004
Sweet Vernal | E4-Sv | 0.02 | 1.0-0.002
Timothy | E6-Ti | 0.02 | 0.6-0.002

Relative potency value of various lots of non-standardized grass pollen extracts are summarized in Table 2. The acceptable BAU/ml ranges for equivalency to FDA reference for a 100,000 BAU/ml product are 69,900-143,100 at n=3, 73,300-136,400 at n=4 and 75,800-132,000 at n=5. Acceptable equivalency ranges for a 10,000 BAU/ml product are 6,990-14,310 at n=3, 7,330-13,640 at n=4 and 7,580-13,200 at n=5 (n=number of tests performed).

TABLE 2
BAU/ml Estimate of Non-standardized Grass Pollen Allergenic Extracts
Commercially Distributed by Antigen Laboratories, Inc.

50% v/v Glycerinated Extract | w/v | Lot # | N | BAU/ml Range
Redtop | 1:20 | R19101193 | 3 | 92,350-109,340
Redtop | 1:33 | R19022194 | 3 | 30,410-51,830
Meadow Fescue | 1:20 | F09062493 | 3 | 196,270-308,200
Meadow Fescue | 1:33 | F09092993 | 3 | 141,670-295,730
Bermuda | 1:20 | B29121393 | 3 | 11,263-13,359
Bermuda | 1:33 | B29013194 | 3 | 6,299-10,195
Kentucky Bluegrass | 1:20 | J05012494 | 3 | 73,580-116,880
Kentucky Bluegrass | 1:33 | J05120793 | 4 | 32,220-57,940
Sweet Vernal | 1:20 | S37031594 | 3 | 107,300-191,360
Sweet Vernal | 1:20 | S37042495 | 3 | 93,180-107,120
Perennial Rye | 1:20 | R21032194 | 3 | 82,600-136,070
Perennial Rye | 1:33 | R21011393 | 3 | 65,770-127,700
Timothy | 1:20 | T18013194 | 3 | 81,320-99,470
Timothy | 1:20 | T18121994 | 3 | 45,340-68,990
Orchard | 1:20 | O12032593 | 5 | 83,690-110,590
Orchard | 1:33 | O12011994 | 4 | 56,550-77,150

INDICATIONS AND USAGE
Allergenic extract is indicated for diagnostic testing and treatment (immunotherapy) of patients whose histories indicate allergic symptoms upon natural exposure to grass allergens. Confirmation is determined by skin testing. 10,000 BAU/ml extracts are intended for percutaneous testing. If negative, 100,000 BAU/ml products can be used for percutaneous test. Dilutions made from 10,000 BAU/ml products are indicated for immunotherapy of previously untreated patients. If 10,000 BAU/ml product is tolerated and symptoms persist, dilutions made from 100,000 BAU/ml can be administered. Standardized Grass Pollen extracts labeled in Bioequivalent Allergy Units (BAU/ml) are not interchangeable with grass pollen extracts labeled In Allergy Units (AU/ml) or with non-standardized grass pollen extracts.

CONTRAINDICATIONS
Do not administer in the presence of diseases characterized by bleeding diathesis. Individuals with autoimmune disease may be at risk of exacerbating symptoms of underlying disease, possibly due to routine immunization. Recent myocardial infarction patients may not tolerate immunotherapy. Children with nephrotic syndrome probably should not receive injections due to a possibility of immunization causing exacerbation of their nephrotic disease.
Standardized Grass Pollen extract is not intended for the treatment of patients who do not experience allergic symptoms upon natural exposure to the allergen.
Allergenic extracts are not intended for diagnosing patients who do not manifest immediate hypersensitivity reactions to the allergenic extract when skin tested.

WARNINGS
Refer to boxed "WARNINGS", "PRECAUTIONS", "ADVERSE REACTIONS" and "OVERDOSAGE" sections for additional information on serious adverse reactions and steps to be taken, if any occur.
Extreme caution is necessary when using diagnostic skin tests or injection treatment in highly sensitive patients who have experienced severe symptoms or anaphylaxis by natural exposure, or during previous skin testing or treatment. IN THESE CASES THE POTENCY FOR SKIN TESTS AND THE ESCALATION OF THE TREATMENT DOSE MUST BE ADJUSTED TO THE PATIENTS SENSITIVITY AND TOLERANCE.
Benefit versus risk needs to be evaluated in steroid dependent asthmatics, patients with unstable asthma or patients with underlying cardiovascular disease.
Injections should never be given intravenously. A 5/8 inch, 25 gauge needle on a sterile syringe allows deep subcutaneous injection. Withdraw plunger slightly after inserting needle to determine if a blood vessel has been entered.
Proper measurement of dose and caution in making injection will minimize reactions.
Adverse reactions to allergenic extracts are usually apparent within 20-30 minutes following injection of immunotherapy.
Extract should be temporarily withheld or dosage reduced in case of any of the following conditions: 1) flu or other infection with fever; 2) exposure to excessive amounts of allergen prior to injection; 3) rhinitis and/or asthma exhibiting severe symptoms; 4) adverse reaction to previous injection until cause of reaction has been evaluated by physician supervising patient's immunotherapy program.

PRECAUTIONS
General:
Immunotherapy must be given under physician's supervision. Sterile solutions, vials, syringes, etc. must be used. Aseptic technique must be observed in making dilutions from stock concentrates. The usual precautions in administering allergenic extracts are necessary, refer to boxed WARNINGS and "WARNINGS" section. Sterile syringe and needle must be used for each individual patient to prevent transmission of serum hepatitis, Human Immunodeficiency Virus (HIV) and other infectious agents.
Epinephrine 1:1000 should be available. Refer to "OVERDOSAGE" section for description of treatment for anaphylactic reactions.
Information for Patients:
Patient should remain under observation of a nurse, physician, or personnel trained in emergency measures for at least 20 minutes following immunotherapy injection. Patient must be instructed to report any adverse reactions that occur within 24 hours after injection. Possible adverse reactions include unusual swelling and/or tenderness at injection site, rhinorrhea, sneezing, coughing, wheezing, shortness of breath, nausea, dizziness, or faintness. Immediate medical attention must be sought for reactions that occur during or after leaving physician's office.
Pregnancy Category C:
Animal reproduction studies have not been conducted with allergenic extracts. It is not known whether allergenic extracts cause fetal harm during pregnancy or affect reproductive capacity. A systemic reaction to allergenic extracts could cause uterine contractions leading to spontaneous abortion or premature labor. Allergenic extracts should be used during pregnancy only if potential benefit justifies potential risk to fetus.^6
Nursing Mothers:
It is not known whether allergenic extracts are excreted in human milk. Because many drugs are excreted in human milk, caution should be exercised when allergenic extracts are administered to a nursing woman.
Pediatric Use:
Allergenic extracts have been used routinely in children and no special problems of safety or specific hazard have been found. Children can receive the same dose as adults. Discomfort is minimized by dividing the dose in half and administering injection at two different sites. ^13,14
Carcinogenicity, Mutagenicity, Impairment of Fertility:
Long term animal studies have not been conducted with Standardized Grass Pollen allergenic extracts to evaluate carcinogenicity, mutagenicity or fertility impairment.
Drug Interactions:
Antihistamines. Antihistamines inhibit the wheal and flare reaction. The inhibitory effect of conventional antihistamines varies from 1 day up to 10 days, according to the drug and patient's sensitivity. Long acting antihistamines (e.g., astemizole) may inhibit the wheal and flare for up to forty days.
Imipramines. phenothiazines, and tranquilizers. Tricyclic antidepressants exert a potent and sustained decrease of skin reactions to histamine. This effect may last for a few weeks. Tranquilizers and antiemetic agents of the phenothiazine class have H, antihistaminic activity and can block skin tests.^1
Corticosteroids. Short-term (less than 1 week) administration of corticosteroids at the therapeutic doses used in asthmatic patients does not modify the cutaneous reactivity to histamine, compound 48/80, or allergen. Long-term corticosteroid therapy modifies the skin texture and makes the interpretation of immediate skin tests more difficult.^1
Theophylline. It appears that theophylline need not be stopped prior to skin testing.^1
Beta-blockers. PATIENTS RECEIVING BETA-BLOCKERS MAY NOT BE RESPONSIVE TO EPINEPHRINE OR INHALED BRONCHODILATORS. The following are commonly prescribed BETA-BLOCKERS: Levatol, Lopressor, Propanolol Intersol, Propanolol HCL, Blocadren, Propanolol, Inderal-LA, Visken, Corgard, Ipran, Tenormin, Timoptic. Ophthalmic beta-blockers: Betaxolol, Levobunolol, Timolol, Timoptic. Chemicals that are beta-blockers and may be components of other drugs: Acebutolol, Atenolol, Esmolol, Metoprolol, Nadolol, Penbutolol, Pindolol, Propanolol, Timolol, Labetalol, Carteolol.
Beta-adrenergic agents. Inhaled beta2 agonists in the usual doses used for the treatment of asthma do not usually inhibit allergen-induced skin tests. However, oral terbutaline and parenteral ephedrine were shown to decrease the allergen-induced wheal.
Cromolyn. Cromolyn inhaled or injected prior to skin tests with allergens or degranulating agents does not alter the skin whealing response.^1
Other drugs. Other drugs have been shown to decrease skin test reactivity. Among them, dopamine is the best-documented compound.^1
Specific immunotherapy. A decreased skin test reactivity has been noticed by many authors for patients undergoing specific immunotherapy with pollen extracts, grass pollen allergoids, mite, or hymenoptera venoms, or in professional beekeepers who are spontaneously desensitized. Finally, it was shown that specific immunotherapy in patients treated with ragweed pollen extract induced a decreased late-phase reaction.^1

ADVERSE REACTIONS
Adverse reactions include, but are not limited to urticaria; itching; edema of extremities; respiratory wheezing or asthma; dyspnea; cyanosis; tachycardia; lacrimation; marked perspiration; flushing of face, neck or upper chest; mild persistent clearing of throat; hacking cough or persistent sneezing.
1) Local Reactions
A mild burning immediately after injection is expected; this usually subsides in 10-20 seconds. Prolonged pain or pain radiating up arm is usually the result of intramuscular injection, making this injection route undesirable. Subcutaneous injection is the recommended route.
Small amounts of erythema and swelling at the site of injection are common.
Reactions should not be considered significant unless they persist for at least 24 hours or exceed 50 mm in diameter.
Larger local reactions are not only uncomfortable, but indicate the possibility of a severe systemic reaction if dosage is increased. In such cases dosage should be reduced to the last level not causing reaction and maintained for two or three treatments before cautiously increasing.
Large, persistent local reactions or minor exacerbations of the patient's allergic symptoms may be treated by local cold applications and/or use of oral antihistamines.
2) Systemic Reactions
Systemic reactions range from mild exaggeration of patient's allergic symptoms to anaphylactic reactions.^12 Very sensitive patients may show a rapid response. It cannot be overemphasized that, under certain unpredictable combinations of circumstances, anaphylactic shock is always a possibility. Fatalities are rare but can occur.^16 Other possible systemic reaction symptoms are fainting, pallor, bradycardia, hypotension, angioedema, cough, wheezing, conjunctivitis, rhinitis, and urticaria.^8,9
Careful attention to dosage and administration limit such reactions. Allergenic extracts are highly potent to sensitive individuals and OVERDOSE could result in anaphylactic symptoms. Therefore, it is imperative that physicians administering allergenic extracts understand and prepare for treatment of severe reactions. Refer to "OVERDOSAGE" section.

OVERDOSAGE
Refer to "WARNINGS", "PRECAUTIONS", and "ADVERSE REACTIONS" sections for signs and symptoms of overdose.
If a systemic or anaphylactic reaction does occur, apply tourniquet above the site of allergenic extract injection and inject intramuscularly or subcutaneously 0.3 to 0.5 ml of 1:1000 Epinephrine-hydrochloride into the opposite arm or gluteal area. Repeat dose in 5-10 minutes if necessary. Loosen tourniquet briefly at 5 minute intervals to prevent circulatory impairment. Discontinue use of the tourniquet after hour.
The epinephrine HCL 1:1000 dose for infants to 2 years is 0.05 to 0.1 ml; for children 2 to 6 years it is 0.15 ml; for children 6 to 12 years it is 0.2 ml. Symptoms of progressive anaphylaxis include airway obstruction and/or vascular collapse. After administration of epinephrine, profound shock and vasomotor collapse should be treated with intravenous fluids and possibly vasoactive drugs. Monitor airways for obstruction. Oxygen should be given by mask if indicated.
Antihistamines, H2 antagonist, bronchodilators, steroids and theophylline may be used as indicated after giving adequate epinephrine and circulatory support.^12
Patients who have been taking a beta-blocker may be unresponsive to epinephrine or beta-adrenergic drugs (Alupent). These drugs should be administered even though a beta-blocker may have been taken. The following treatment will be effective whether or not patient is taking a beta-blocker: Aminophylline IV, slow push or drip, Atrovent (Ipratropium bromide) Inhaler, 3 inhalations repeated, Atropine, 0.4 mg/ml, 0.75 to 1.5 ml lM or IV, Solu-Cortef, 100-200 mg IM or IV, Solu-Medrol, 125 mg IM or IV, Glucagon, 0.5-1 mg IM or IV, Benadryl, 50 mg IM or IV, Cimetidine, 300 mg IM or IV, Oxygen via ambu bag.

DOSAGE AND ADMINISTRATION
Refer to "STORAGE" section for proper storage condition for allergenic extract.
Parenteral drug products should be inspected visually for particulate matter and discoloration prior to administration, whenever solution and container permit. Some allergenic extracts naturally precipitate.
Precaution is necessary when using grass pollen extract mixtures. Potency may be additive and may equal the total potency of the grass pollen extracts in the mixture. Careful attention to container label and/or package insert in regard to BAU/ml of grass pollen extracts from which mixture is derived is important.
Physicians undertaking immunotherapy should be concerned with patient's degree of sensitivity. The initial dilution of allergenic extract, starting dose and progression of dosage must be carefully determined on the basis of the patient's history and results of skin tests. (SEE "INDICATIONS AND USAGE" section.) Strongly positive skin tests may be risk factors for systemic reactions. Less aggressive immunotherapy schedules may be indicated for such patients.
PRICK-PUNCTURE TESTING: To identify grass sensitive individuals and as a safety precaution, it is recommended that a prick or puncture test be performed prior to initiating very dilute intradermal testing. Prick (puncture) testing is performed by placing a drop of extract on skin and puncturing skin through the drop with a prick-puncture device. The most satisfactory sites on the back for skin testing are from posterior axillary fold to 2.5 cm from the spinal column, and from the top of the scapula to the lower rib margins. The best areas on the arms are the volar surfaces from the axilla to 2.5 or 5 cm above the wrist, skipping the anticubital space. It is recommended that 10,000 BAU/ml Standardized Grass Pollen extract be used for initial puncture testing because 100,000 BAU/ml extracts produce very large puncture reactions in highly reactive individuals.^18 A positive reaction is approximately 10-15 mm erythema with 2.5 mm wheal.
Smaller, less conclusive reactions may be considered positive in conjunction with a definitive history of symptoms on exposure to allergen. Less sensitive individuals can be tested intradermally with appropriately diluted extract. (See Intradermal Testing.)
A positive control using histamine phosphate identifies patients whose skin may not react due to medications, metabolic or other reasons. A negative control (50% glycerine for prick-puncture testing) would exclude false-positive reactions due to ingredients in diluent or patients who have dermatographism.

SERIAL DILUTIONS
APPROXIMATE BAU/ml RESULTING FROM 1:10 DILUTION
OF ALLERGENIC EXTRACT CONCENTRATE

DILUTION # | DILUTION EXPONENT | 100,000 BAU/ML | 10,000 BAU/ML
1 | 10^-1 | 10,000 | 1,000
2 | 10^-2 | 1,000 | 100
3 | 10^-3 | 100 | 10
4 | 10^-4 | 10 | 1
5 | 10^-5 | 1 | 0.1
6 | 10^-6 | 0.1 | 0.01
7 | 10^-7 | 0.01 | 0.001
8 | 10^-8 | 0.001 | 0.0001
9 | 10^-9 | 0.0001 | 0.00001
10 | 10^-10 | 0.00001 | 0.000001

SERIAL DILUTIONS
APPROXIMATE BAU/ml RESULTING FROM 1:5 DILUTION
OF ALLERGENIC EXTRACT CONCENTRATE

DILUTION # | DILUTION EXPONENT | 100,000 BAU/ML | 10,000 BAU/ML
1 | 5^-1 | 20,000 | 2,000
2 | 5^-2 | 4,000 | 400
3 | 5^-3 | 800 | 80
4 | 5^-4 | 160 | 16
5 | 5^-5 | 32 | 3.2
6 | 5^-6 | 6.4 | 0.64
7 | 5^-7 | 1.28 | 0.128
8 | 5^-8 | 0.256 | 0.0256
9 | 5^-9 | 0.0512 | 0.00512
10 | 5^-10 | 0.01024 | 0.001024
11 | 5^-11 | 0.002048 | 0.0002048

INTRADERMAL TESTING: Upper to lower arm are the usual locations for skin testing. A sterile, disposable syringe and needle is used for each extract tested. Intracutaneous test dilutions should be made with aqueous diluent. Three-fold, five-fold or ten-fold dilutions may be prepared from stock concentrates. (1) Start testing with the most dilute allergenic extract concentration. (2) A volume of 0.01-0.02 ml should be injected slowly into the superficial skin layers making a small bleb (superficial wheal). (3) For patients with grass sensitivity based on puncture reactivity, a concentration of approximately 0.02 BAU/ml (10,000 BAU/ml 5^-8 or 10^-6 or 100,000 BAU/mI 5^-10 or 10^-7 dilution) should be used for initial skin testing ("CLINICAL PHARMACOLOGY", Table 1B). Reactions to skin testing are graded 0 to 4+ according to size of wheal and erythema produced (refer to chart below). The reactions should be read after fifteen minutes.
EVALUATION OF SKIN REACTIONS

GRADE | mm ERYTHEMA | mm WHEAL
0 | less than 5 | less than 5
+/- | 5-10 | 5-10
1+ | 11-20 | 5-10
2+ | 21-30 | 5-10
3+ | 31-40 | 10-15 or with pseudopods
4+ | greater than 40 | greater than 15 or with many pseudopods

If after twenty minutes no skin reaction is observed, continued testing using increments of the concentration until a reaction of 5-10 mm wheal and 10-30 mm erythema is obtained, or a concentration of 5^-2 or 10^-1 if using 10,000 BAU/ml extract has been tested. A positive control of histamine phosphate and a negative control of 50% v/v glycerine diluted with diluent to 5^-2 (1:25) or 10^-1 (1:10) dilution, should be included in interpretation of intradermal testing.^1
INTRADERMAL TESTING - SKIN ENDPOINT TITRATION: Patient's degree of sensitivity and the initial dose of allergen to be used in immunotherapy can be quantitated using five-fold dilutions of allergenic extract for intracutaneous testing. Intracutaneously inject 0.01-0.02 ml of the test allergen to form a 4 mm diameter superficial wheal. A concentration of 0.02 BAU/ml is a safe initial dilution ("CLINICAL PHARMACOLOGY", Table 1B). When a sequence of five-fold or ten-fold dilutions of an allergen are injected, the endpoint is determined by noting the dilution that first produces a wheal and erythema (15 minutes after injection) that is 2 mm larger than wheals with erythema produced by weaker, nonreacting dilutions (5mm negative wheal). The endpoint dilution is used as a starting dose concentration for immunotherapy.
IMMUNOTHERAPY: Normally, immunotherapy can be started with 0.15 ml of the dilution of allergenic extract causing the endpoint reaction. In any allergic patient, a safe starting dose can be determined by finding the first dose by intradermal skin testing producing a 1+ reaction or the dilution producing the skin endpoint.
Increasing doses of 5-20% increments can be administered providing initial or preceding dose is tolerated without significant local reactions. The rate of increase in dosage in the early stages of treatment with highly diluted extracts is usually more rapid than the rate of increase possible with more concentrated extracts. This schedule is intended only as a guide and must be modified according to the reactivity of the individual patient. Physicians must proceed cautiously in the treatment of highly sensitive patients who develop large local or systemic reactions.
Some patients may tolerate larger doses of the allergenic extract depending on patient response.^3 Because diluted extracts lose activity on storage, the first dose from a more concentrated vial should be the same or less than the previous dose.^4,7
Dosages progressively increase according to the tolerance of the patient at intervals of one to seven days until: (1) the patient achieves relief of symptoms; (2) induration at the site of injection is no larger than 50 mm in 36 to 48 hours; (3) a maintenance dose is reached (the largest dose tolerated by the patient that relieves symptoms without undesirable local or systemic reactions). This maintenance dose may be continued at regular intervals perennially. It may be necessary to adjust the progression of dosage downward to avoid local and constitutional reactions.^2
The usual duration of treatment has not been established. A period of two or three years on immunotherapy constitutes an average minimum course of treatment.
SWITCHING FROM NON-STANDARDIZED TO STANDARDIZED GRASS POLLEN EXTRACT: Caution is imperative when switching from non-standardized grass pollen to Standardized Grass Pollen extracts. Standardized Grass Pollens may have equal, greater, or lesser potency than non-standardized grass pollen ("CLINICAL PHARMACOLOGY", Table 2).
Patient skin testing, utilizing side by side endpoint titration, can be used to determine the relative potency of standardized to non-standardized grass pollen extract. Based on their relative potency, a dose equipotent to the non-standardized extract can be administered. For example, a five fold dilution of standardized extract producing the identical skin responses as the non-standardized grass pollen concentrate would require five fold reduction of dose. (If patient had been receiving 0.1 ml of non-standardized extract concentrate, then they should now receive 0.1 ml of 1:5 dilution of the Standardized Grass Pollen extract.)
Alternately, standardized extract or a mix containing Standardized Grass Pollen extract can be administered as though the patient were newly beginning immunotherapy; i.e. the patient can be skin tested to determine a safe initial dose.

HOW SUPPLIED
Standardized Grass Pollen allergenic extract concentration is expressed in BAU/ml. It is supplied in 100,000 BAU/ml and 10,000 BAU/ml in 10, 30 and 50 ml containers. Standardized Bermuda Grass is only available as 10,000 BAU/ml concentrate. Stock mixtures of Standardized Grass Pollens and mixtures of standardized and non-standardized grass pollens are available at various concentrations. Extracts in 5 ml dropper bottles are available for prick-puncture testing. To insure maximum potency for the entire dating period, all stock concentrates contain 50% v/v glycerine.

STORAGE
Store all stock concentrates and dilutions at 2-8 degrees C. Keep at this temperature during office use. The expiration date of allergenic extracts is listed on the container label. Dilutions of allergenic extracts containing less than 50% v/v glycerine are less stable than those containing at least 50% v/v glycerine. If loss of potency is suspected, potency can be checked using side by side skin testing with freshly prepared dilutions of equal concentration on individuals with known sensitivity to the allergen.

REFERENCES
1. Bousquet, Jean: "In vivo methods for study of allergy: Skin tests" Third Edition, Allergy Principles and Practice, C.V. Mosby Co., Vol. I, Chap. 19, pp 419-436, 1988.
2. Matthews, K., et al; Rhinitis, Asthma and the Other Allergic Diseases, NIAID Task Force Report, U.S. Dept. HEW, NIH Publication No. 79-387, Chapter 4, pp. 213-217, May 1979.
3. Ishizaka, K.: Control of IgE Synthesis, Third Edition, Allergy Principles and Practices, C.V. Mosby Co.,Vol. I, Chap. 4, p. 52, 1988.
4. Nelson, H.S.: "The Effect of Preservatives and Dilution on the Deterioration of Russian Thistle (Salsola pestifer), a pollen extract." The Journal of Allergy and Clinical Immunology, Vol. 63, No.6, pp. 417-425, June 1979.
5. Rocklin, R.E., Sheffer, A.L., Grainader, D.K. and Melmon, K.: "Generation of antigen-specific suppressor cells during allergy desensitization", New England Journal of Medicine, Vol. 302, pp. 1213-1219, May 29,1980.
6. Seebohm, P.M., et al: Panel on Review of Allergenic Extracts, Final Report, Food and Drug Administration, pp. 9-48, March 13, 1981.
7. Stevens, E.; Cutaneous Tests, Regulatory Control and Standardization of Allergenic Extracts, First International Paul Ehrlich Seminar, Frankfurt, Germany, pp. 133-138, May 20-22,1979.
8. Van Metre, T., Adkinson, N., Amodio, F., Lichtenstein, L., Mardinay, M., Norman, P., Rosenberg, G., Sobotka, A., Valentine, M.: "A Comparative Study of the Effectiveness of the Rinkel Method and the Current Standard Method of Immunology for Ragweed Pollen Hay Fever," The Journal of Clinical Allergy and Immunology, Vol. 66, No. 6, p. 511, December 1980.
9. Wasserman, S.: The Mast Cell and the Inflammatory Response. The Mast Cell its role in health and disease. Proceedings of an International Symposium, Davos, Switzerland, Pitman Medical Publishing Co., pp. 9-20, 1979.
10. Perelmutter, L.: IgE Regulation During Immunotherapy of Allergic Diseases. Annals of Allergy, Vol. 57, August 1986.
11. Baer, H., Anderson, M.C., Turkeltaub, P.C.: Allergenic Extracts, Third Edition, Allergy Principles and Practice, C.V. Mosby Co., Vol. I, Chap. 17, 1988.
12. Wasserman, S., Marquart, D.: Anaphylaxis, Third Edition, Allergy Principles and Practice, C.V. Mosby Co., Vol. 1, Chap. 58, pp. 1365-1376, 1988.
13. Bullock, J., Frick, O.: Mite Sensitivity in House Dust Allergic Children, Am. J. Dis. Child., pp.123-222, 1972.
14. Willoughby, J.W.: Inhalant Allergy Immunotherapy with Standardized and Nonstandardized Allergenic Extracts, American Academy of Otolaryngology-Head and Neck Surgery: Instructional Courses, C.V. Mosby Co., Vol. 1, Chapter 15, September 1988.
15. Holgate, S.T., Robinson, C., Church, Mike: Mediators of Immediate Hypersensitivity, Third Edition, Allergy Principles and Practice, C.V. Mosby Co., Vol. I and II, pp 135-163, 1988.
16. Reid, Michael J., Lockey, Richard F., Turkeltaub, Paul C., M.D., Platts-Mills, Thomas: "Survey of Fatalities from Skin Testing and Immunotherapy 1985-1989", Journal of Allergy and Clinical Immunology, Vol. 92, No.1, pp. 6-15, 1993.
17. Turkeltaub, Paul C., M.D., Rastogi, Saresh, Ph.D.: Center for Biologics Research and Review. "Quantitative Intradermal Procedure for Evaluation of Subject Sensitivity of Standardized Allergenic Extracts and for Assignment of Bioequivalent Allergy Units to Reference Preparations Using the ID50EAL Method (Intradermal Dilution for 50 mm Sum of Erythema Determines Bioequivalent ALlergy Units), Nov., 1994.
18. Turkeltaub, Paul C., M.D.: "Standardized Extracts in Practice", Immunotherapy, A Practical Guide to Current Procedures, Sponsored by American Academy of Allergy and Immunology, 1994.